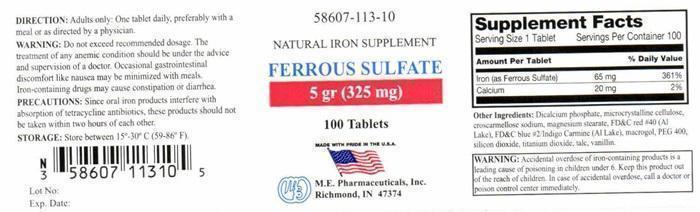 DRUG LABEL: FERROUS SULFATE
NDC: 58607-113 | Form: TABLET
Manufacturer: MARTIN EKWEALOR PHARMACEUTICALS, INC.
Category: otc | Type: HUMAN OTC DRUG LABEL
Date: 20140925

ACTIVE INGREDIENTS: FERROUS SULFATE 65 mg/1 1; CALCIUM 20 mg/1 1
INACTIVE INGREDIENTS: CALCIUM PHOSPHATE, DIBASIC, ANHYDROUS; CELLULOSE, MICROCRYSTALLINE; CROSCARMELLOSE SODIUM; MAGNESIUM STEARATE; FD&C RED NO. 40; FD&C BLUE NO. 2; POLYETHYLENE GLYCOLS; POLYETHYLENE GLYCOL 400; SILICON DIOXIDE; TITANIUM DIOXIDE; TALC; VANILLIN

Active Ingredients

Supplemental Facts

Serving Size 1 Tablet Servings per Container 100

Amount Per Tablet % Daily Value

Iron (as Ferrous Sulfate) 65 mg 361%

Calcium 20 mg 2%

Purpose

NATURAL IRON SUPPLEMENT

Keep out of reach of children.

WARNING: Accidental overdose of iron-containing products is a leading cause of poisoning in children under 6. Keep this product out of the reach of children. In case of accidental overdose, call a doctor or poison control center immediately.

Indications and Usage

NATURAL IRON SUPPLEMENT. The treatment of any anemic condition should be under the advise and supervision of a doctor.

WARNINGS: PRECAUTIONS:

WARNING: Do not exceed recommended dosage. The treatment of any anemic condition should be under the advice and supervision of a doctor. Occasional gastrointestinal discomfort like nausea may be minimized with meals. Iron-containing drugs may cause constipation or diarrhea.
PRECAUTIONS: Since oral iron products interfere with absorption of tetracycline antibiotics, these products should not be taken within two hours of each other.

DIRECTIONS:

Adults only. One tablet daily, preferably with a meal or as directed by a physician.

Other Ingredients:

Dicalcium phosphate, microcrystalline cellulose, croscarmellose sodium, magnesium stearate, FD and C red #40 (AL Lake), FD and C blue #2/Indigo Carmine (Al Lake), macrogol, PEG 400, silicon dioxide, titanium dioxide, talc, vanillin.

STORAGE:

Store between 15° - 30° C (59° -86° F)

FERROUS SULFATE Product Label

58607-113-10
NATURAL IRON SUPPLEMENT
FERROUS SULFATE
5 gr (325 mg)
100 Tablets
MADE WITH PRIDE IN THE U.S.A.
M.E. Pharmaceuticals, Inc.
Richmond, IN 47374
Lot No:
Exp Date: